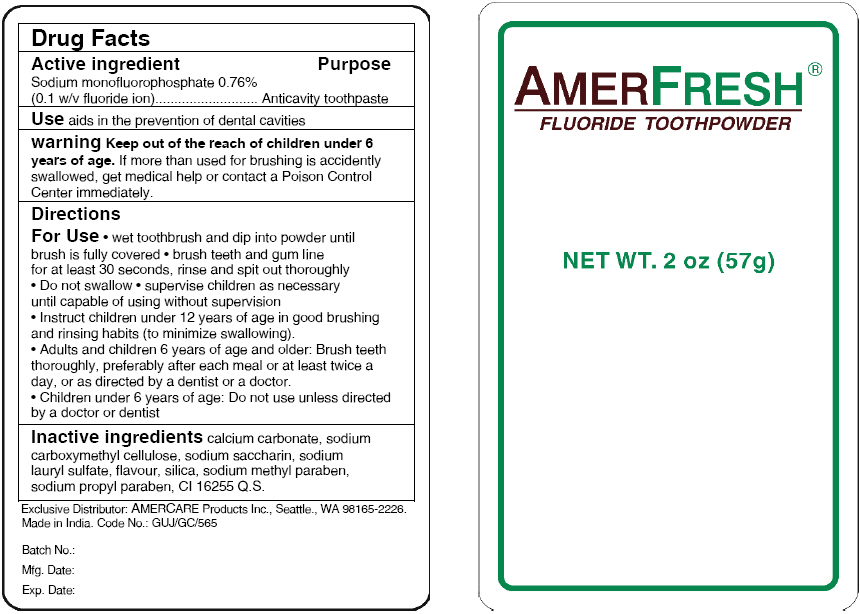 DRUG LABEL: AmerFresh
NDC: 51460-1113 | Form: POWDER, DENTIFRICE
Manufacturer: Amercare Products, Inc.
Category: otc | Type: HUMAN OTC DRUG LABEL
Date: 20130111

ACTIVE INGREDIENTS: Sodium Monofluorophosphate 0.4332 g/57 g
INACTIVE INGREDIENTS: calcium carbonate; carboxymethylcellulose sodium; saccharin sodium; sodium lauryl sulfate; hydrated silica; methylparaben sodium; propylparaben sodium

AmerFresh®
Fluoride Toothpowder

Drug Facts

Active ingredient

Sodium monofluorophosphate 0.76% (0.1 w/v fluoride ion)

Purpose

Anticavity toothpaste

Use

aids in the prevention of dental cavities

warning

KEEP OUT OF REACH OF CHILDREN

Keep out of the reach of children under 6 years of age. If more than used for brushing is accidently swallowed, get medical help or contact a Poison Control Center immediately.

Directions For Use

- wet toothbrush and dip into powder until brush is fully covered
- brush teeth and gum line for at least 30 seconds, rinse and spit out thoroughly
- Do not swallow
- supervise children as necessary until capable of using without supervision
- Instruct children under 12 years of age in good brushing and rinsing habits (to minimize swallowing).
- Adults and children 6 years of age and older: Brush teeth thoroughly, preferably after each meal or at least twice a day, or as directed by a dentist or a doctor.
- Children under 6 years of age: Do not use unless directed by a doctor or dentist

Inactive ingredients

calcium carbonate, sodium carboxymethyl cellulose, sodium saccharin, sodium lauryl sulfate, flavour, silica, sodium methyl paraben, sodium propyl paraben, CI 16255 Q.S.

Exclusive Distributor: AMERCARE Products Inc., Seattle., WA 98165-2226.

PRINCIPAL DISPLAY PANEL - 57 g Packet Label

AMERFRESH®
FLUORIDE TOOTHPOWDER

NET WT. 2 oz (57g)